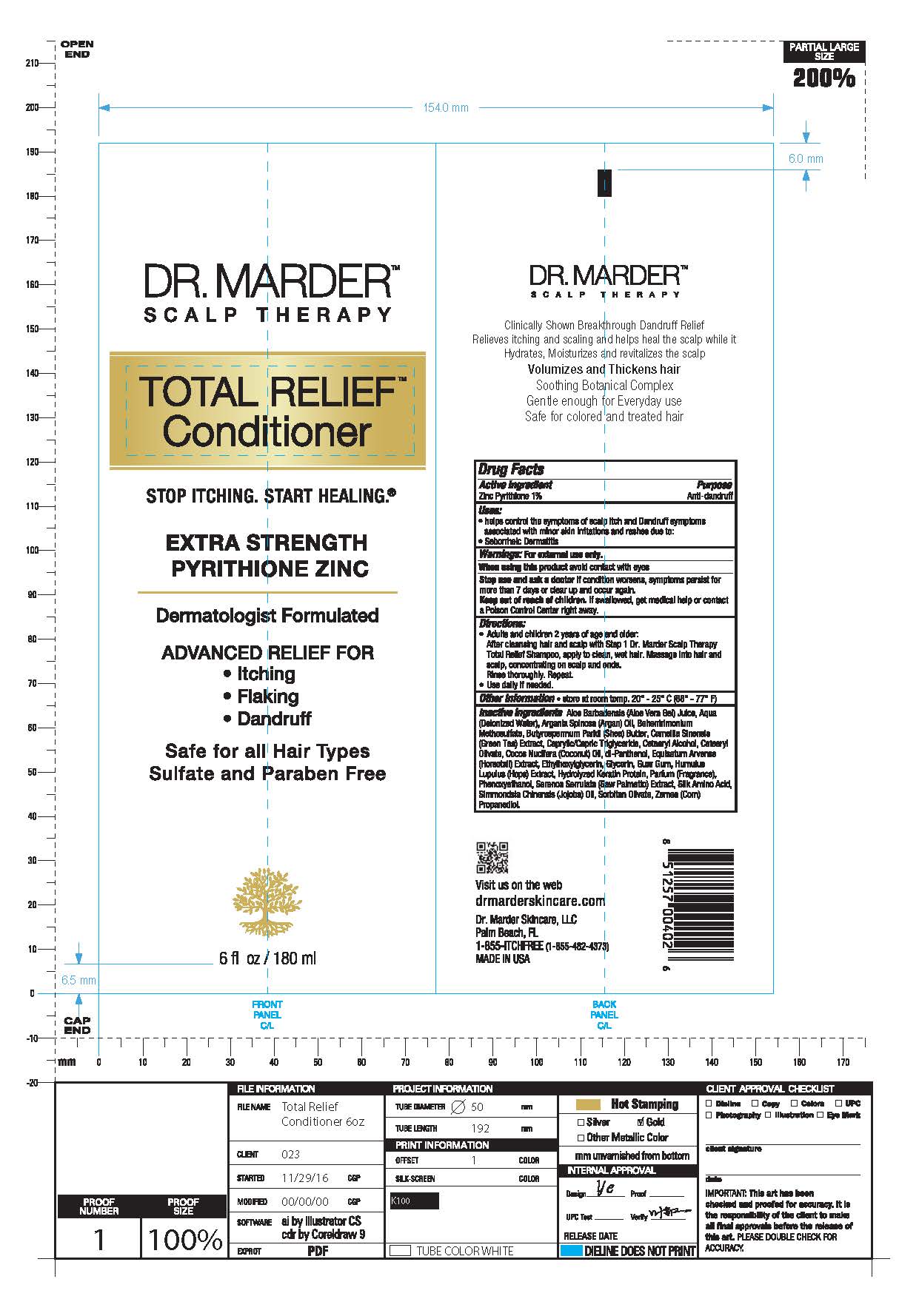 DRUG LABEL: Zinc Pyrithione
NDC: 71516-002 | Form: SHAMPOO
Manufacturer: Dr Marder Skincare LLC
Category: otc | Type: HUMAN OTC DRUG LABEL
Date: 20191102

ACTIVE INGREDIENTS: PYRITHIONE ZINC 1 g/100 mL
INACTIVE INGREDIENTS: CETOSTEARYL ALCOHOL; EQUISETUM ARVENSE BRANCH; GLYCERIN; GUAR GUM; HUMULUS LUPULUS STEM; AMINO ACIDS, SILK; BEHENTRIMONIUM METHOSULFATE; PANTHENOL; AMINO ACIDS, HAIR KERATIN; CORN; ARGANIA SPINOSA LEAF; PHENOXYETHANOL; SAW PALMETTO; SIMMONDSIA CHINENSIS LEAF; SORBITAN OLIVATE; SHEA BUTTER; CAPRYLIC/CAPRIC/LAURIC TRIGLYCERIDE; CETEARYL OLIVATE; COCONUT OIL; ETHYLHEXYLGLYCERIN; ALOE VERA LEAF; WATER; CAMELLIA SINENSIS SEED OIL

Dr. Marder Scalp Therapy Total Relief Conditioner

Keep out of reach of children. if swallowed, get medical help or contact Poison Control Center Right Away

PURPOSE

Anti-Dandruff

WARNINGS

For external use only. When using this product avoid contact with eyes.

INDICATIONS AND USAGE

- Helps control the symptoms of scalp itch and Dandruff symptoms associated with minor skin irritations and rashes due to:
- Seborrheic Dermatitis

ACTIVE INGREDIENT

Zinc Pyrithione 1%

DOSAGE AND ADMINISTRATION

After cleansing hair and scalp with Step 1 Dr. Marder Scalp Therapy Total Relief Shampoo, apply to clean, wet hair. Massage into hair and scalp, concentrating on scalp and ends. Rinse thoroughly. Repeat. Use Daily if needed.

INACTIVE INGREDIENT

CAMELLIA SINENSIS SEED OIL

GLYCERIN

GUAR GUM

HUMULUS LUPULUS STEM

AMINO ACIDS, SILK

BEHENTRIMONIUM METHOSULFATE

PANTHENOL

AMINO ACIDS, HAIR KERATIN

CORN

ARGANIA SPINOSA LEAF

PHENOXYETHANOL

SAW PALMETTO

SIMMONDSIA CHINENSIS LEAF

SORBITAN OLIVATE

SHEA BUTTER

CAPRYLIC/CAPRIC/LAURIC TRIGLYCERIDE

CETEARYL OLIVATE

COCONUT OIL

ETHYLHEXYLGLYCERIN

ALOE VERA LEAF

WATER

CETOSTEARYL ALCOHOL

EQUISETUM ARVENSE BRANCH